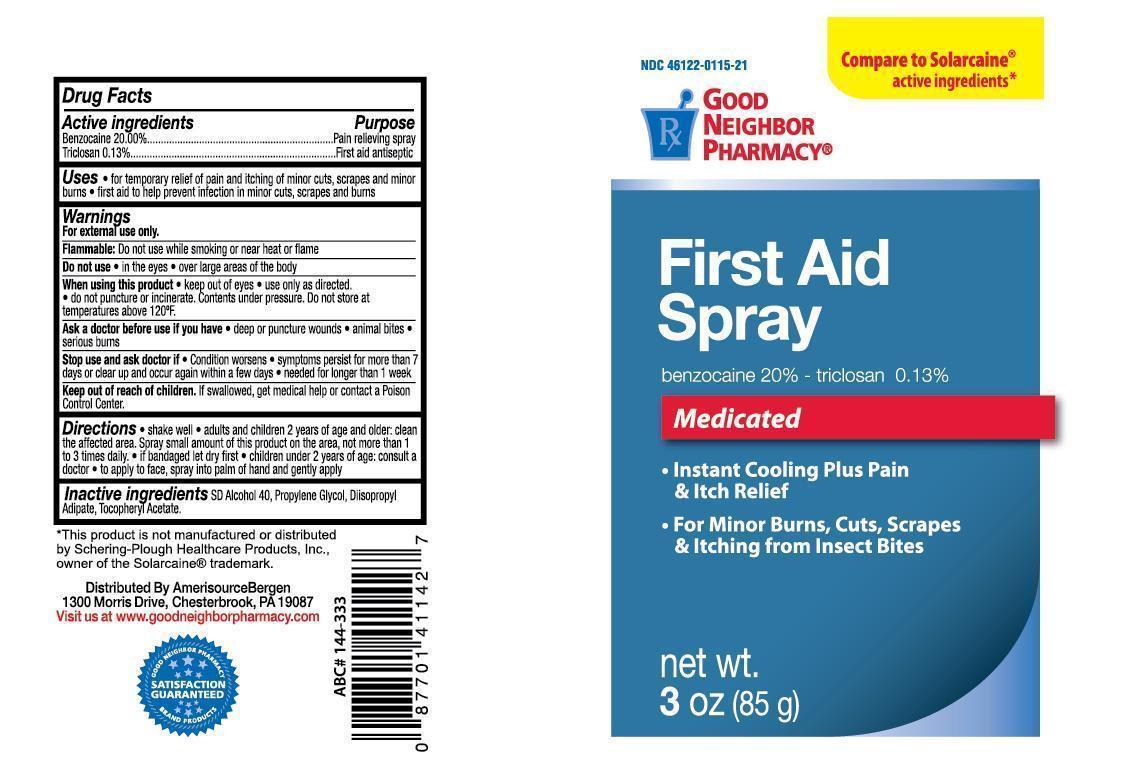 DRUG LABEL: Good Neighbor Pharmacy First Aid
NDC: 46122-115 | Form: AEROSOL, SPRAY
Manufacturer: AmerisourceBergen Drug Corporation
Category: otc | Type: HUMAN OTC DRUG LABEL
Date: 20150427

ACTIVE INGREDIENTS: BENZOCAINE 20 g/100 g; TRICLOSAN 130 mg/100 g
INACTIVE INGREDIENTS: .ALPHA.-TOCOPHEROL ACETATE; PROPYLENE GLYCOL; ALCOHOL; DIISOPROPYL ADIPATE

Good Neighbor Pharmacy First Aid Spray

Drug Facts

Active ingredients

Benzocaine 20.00%

Triclosan 0.13%

Purpose

Pain relieving spray

First aid antiseptic

Uses

- for temporary relief of pain and itching of minor cuts, scrapes and minor burns
- first aid to help prevent infection in minor cuts, scrapes and burns

Warnings

For external use only.

Flammable: Do not use while smoking or near heat or flame

Do not use

- in the eyes
- over large areas of the body

When using this product

- keep out of eyes
- use only as directed.
- do not puncture or incinerate. Contents under pressure. Do not store at temperatures above 120°F.

Ask a doctor before use if you have

- deep or puncture wounds
- animal bites
- serious burns

Stop use and ask doctor if

- Condition worsens
- symptoms persist for more than 7 days or clear up and occur again within a few days
- needed for longer than 1 week

Keep out of reach of children.

- If swallowed, get medical help or contact a Poison Control Center.

Directions

- shake well
- adults and children 2 years of age and older: clean the affected area. Spray small amount of this product on the area, not more than 1 to 3 times daily.
- if bandaged let dry first
- children under 2 years of age: consult a doctor
- to apply to face, spray into palm of hand and gently apply

Inactive ingredients

SD alcohol 40, Propylene Glycol, Diisoporpyl Adipate, Tocopheryl Acetate.

* This product is not manufactured or distributed by Schering-Plough Healthcare Products, Inc., ownder of the Solarcaine® trademark.

Distributed by AmerisourceBergen

1300 Morris Drive, Chesterbrook, PA 19087

Visit us as www.goodneighborpharmacy.com